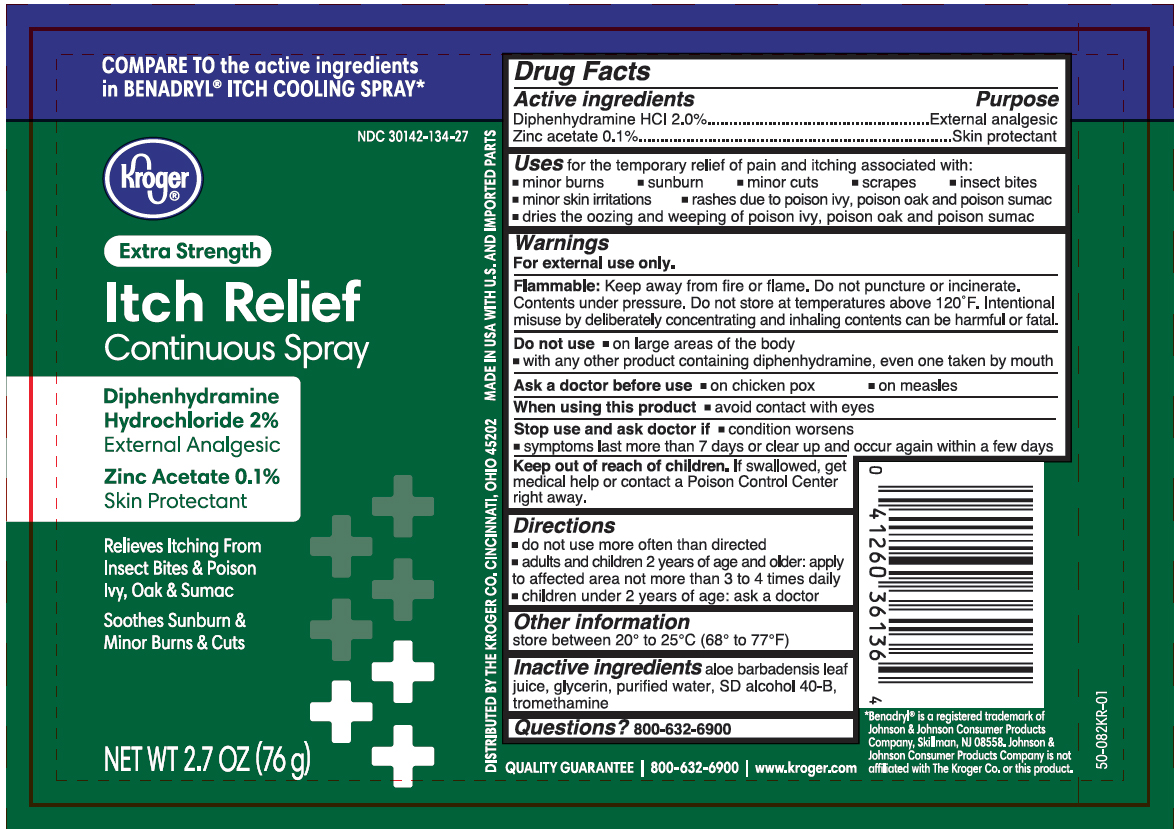 DRUG LABEL: Diphenhydramine HCl and Zinc Acetate
NDC: 30142-134 | Form: SPRAY
Manufacturer: Kroger Co.
Category: otc | Type: HUMAN OTC DRUG LABEL
Date: 20260212

ACTIVE INGREDIENTS: DIPHENHYDRAMINE HYDROCHLORIDE 1.52 g/76 g; ZINC ACETATE 0.076 g/76 g
INACTIVE INGREDIENTS: WATER; GLYCERIN; ALCOHOL; TROMETHAMINE; ALOE VERA LEAF

Kroger Itch Relief Continuous Spray

Active ingredients

Diphenhydramine HCl 2.0%
Zinc acetate 0.1%

Purpose

- External analgesic
- Skin protectant

Uses

for the temporary relief of pain and itching associated with:

- minor burns
- sunburns
- minor cuts
- scrapes
- insect bites
- minor skin irritations
- rashes due to poison ivy, poison oak and poison sumac
- dries the oozing and weeping of poison ivy, poison oak and poison sumac

Warnings

For external use only.

Flammable:

Keep away from fire or flame. Do not puncture or incinerate. Contents under pressure. Do not store at temperature above 120ºF. Intentional misuse by deliberately concentrating and inhaling contents can be harmful or fatal.

Do not use

- on large areas of the body
- with any other products containing diphenhydramine, even one taken by mouth

Ask a doctor before use

- on chicken pox
- on measles

When using this product

- avoid contact with eyes

Stop use and ask doctor if

- condition worsens
- symptoms last more than 7 days or clear up and occur again within a few days

Keep out of reach of children.

If swallowed, get medical help or contact a Poison Control Center right away.

Directions

- do not use more often than directed
- adults and children 2 years of age and older: apply to affected area not more than 3 to 4 times daily
- children under 2 years of age: ask a doctor

Other information

store between 20° to 25°C (68° to 77°F)

Inactive ingredients

aloe barbadensis leaf juice, glycerin, purified water, SD alcohol 40-B, tromethamine

Questions?

800-632-6900

Principal Display Panel

Kroger

Extra Strength

Itch Relief

Continuous Spray

Diphenhydramine

Hydrochloride 2%

External Analgesic

Zinc Acetate 0.1%

Skin Protectant

Relieves Itching from

Insect Bites & Poison

Ivy, Oak & Sumac

Soothes Sunburn &

Minor Burns & Cuts

NET WT 2.7 OZ (76g)